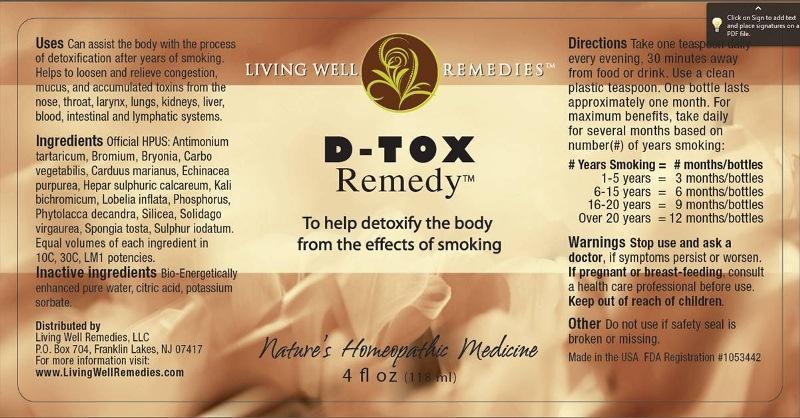 DRUG LABEL: D-TOX Remedy
NDC: 53852-0005 | Form: LIQUID
Manufacturer: Living Well Remedies, LLC
Category: homeopathic | Type: HUMAN OTC DRUG LABEL
Date: 20140508

ACTIVE INGREDIENTS: ANTIMONY POTASSIUM TARTRATE 10 [hp_C]/118 mL; BROMINE 10 [hp_C]/118 mL; BRYONIA ALBA ROOT 10 [hp_C]/118 mL; ACTIVATED CHARCOAL 10 [hp_C]/118 mL; MILK THISTLE 10 [hp_C]/118 mL; ECHINACEA PURPUREA 10 [hp_C]/118 mL; CALCIUM SULFIDE 10 [hp_C]/118 mL; POTASSIUM DICHROMATE 10 [hp_C]/118 mL; LOBELIA INFLATA 10 [hp_C]/118 mL; PHOSPHORUS 10 [hp_C]/118 mL; PHYTOLACCA AMERICANA ROOT 10 [hp_C]/118 mL; SILICON DIOXIDE 10 [hp_C]/118 mL; SOLIDAGO VIRGAUREA FLOWERING TOP 10 [hp_C]/118 mL; SPONGIA OFFICINALIS SKELETON, ROASTED 10 [hp_C]/118 mL; SULFUR IODIDE 10 [hp_C]/118 mL
INACTIVE INGREDIENTS: WATER; CITRIC ACID MONOHYDRATE; POTASSIUM SORBATE

D-TOX Remedy™

DOSAGE AND ADMINISTRATION

Directions: Take one teaspoon daily every evening, 30 minutes away from food or drink. Use a clean plastic teaspoon. One bottle lasts approximately one month. For maximum benefits, take daily for several months based on number (#) of years smoking:

Years Smoking = # months/bottles

1-5 years = 3 months/bottles

6-15 years = 6 months/bottles

16-20 years = 9 months/bottles

over 20 years =12 months/bottles

WARNINGS

Warnings: Stop use and ask a doctor, if symptoms persist or worsen. If pregnant or breast-feeding, consult a health care professional before use.

Keep out of reach of children.

OTHER SAFETY INFORMATION

Other: Do not use if safety seal is broken or missing.

PURPOSE

Uses: Can assist the body with the process of detoxification after years of smoking. Helps to loosen and relieve congestion, mucus, and accumulated toxins from the nose, throat, larynx, lungs, kidneys, liver, blood, intestinal and lymphatic systems.

ACTIVE INGREDIENT

Ingredients: Official HPUS: Antimonium tartaricum, Bromium, Bryonia, Carbo vegetabilis, Carduus marianus, Echinacea purpurea, Hepar sulphuris calcareum, Kali bichromicum, Lobelia inflata, Phosphorus, Phytolacca decandra, Silicea, Solidago virgaurea, Spongia tosta, Sulphur iodatum. Equal volumes of each ingredient in 10C, 30C, LM1 potencies.

INACTIVE INGREDIENT

Inactive ingredients: Bio-Energetically enhanced pure water, citric acid, potassium sorbate.

INDICATIONS AND USAGE

Uses: Can assist the body with the process of detoxification after years of smoking. Helps to loosen and relieve:

- congestion
- mucus
- accumulated toxins from the nose, throat, larynx, lungs, kidneys, liver, blood, intestinal and lymphatic systems.